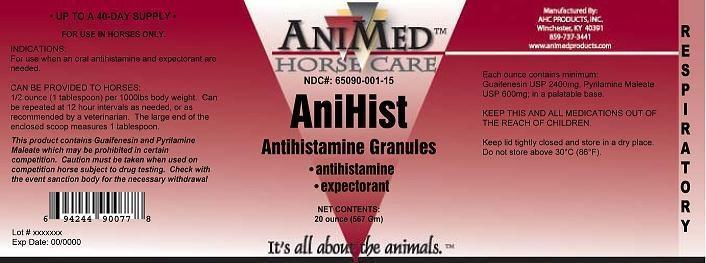 DRUG LABEL: AniHist
NDC: 65090-001 | Form: GRANULE
Manufacturer: AHC Products Inc
Category: animal | Type: OTC ANIMAL DRUG LABEL
Date: 20220121

ACTIVE INGREDIENTS: GUAIFENESIN 2400 mg/28.3 g; PYRILAMINE MALEATE 600 mg/28.3 g

Drug Facts

INDICATIONS AND USAGE

For use when an oral antihistamine and expectorant are needed.

DOSAGE AND ADMINISTRATION

Can be provided to horses: 1/2 ounce (1 tablespoon) per 1000lbs body weight. Can be repeated at 12 hour intervals as needed, or as recommended by a veterinarian.

WARNING
This product contains Guaifenisen and Pyrilamine Maleate which may be prohibited in certain competition. Caution must be taken when used on competition horses subject to drug testing. Check with the event sanction body for the necessary withdrawal time.

KEEP THIS AND ALL MEDICATIONS OUT OF THE REACH OF CHILDREN.
Keep lid tightly closed and store in a dry place. Do not store above 30 C (86F).

ACTIVE INGREDIENT

Each ounce contains minimum:

Guafenisen USP 2400mg, Pyrilamine Maleat USP 600mg

PACKAGE LABEL

NDC 65090-001-15

AniHist

antihistamine

expectorant

Net Contents: 20 ounces (567 gm)